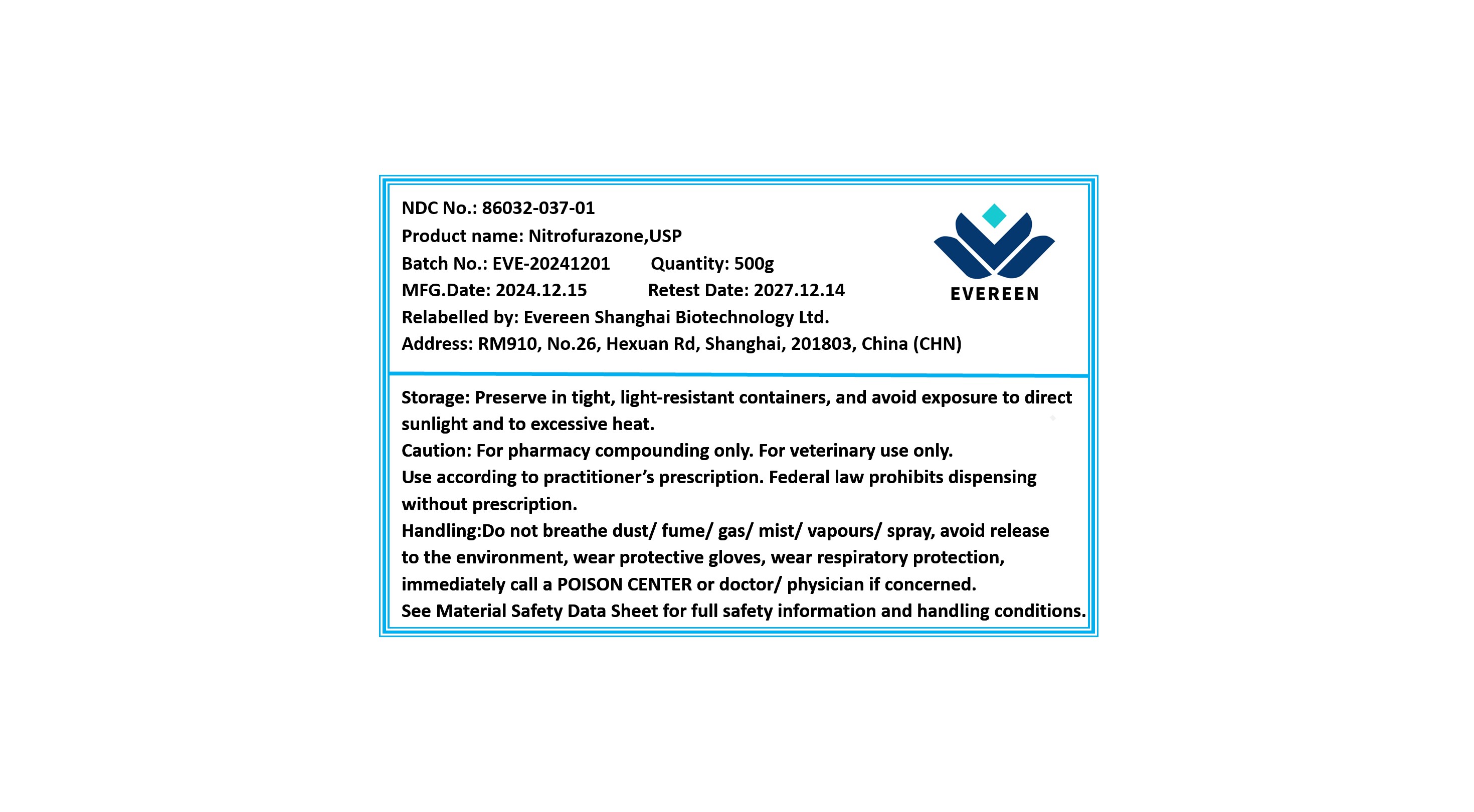 DRUG LABEL: Nitrofurazone
NDC: 86032-037 | Form: POWDER
Manufacturer: Evereen Shanghai Biotechnology Ltd.
Category: other | Type: BULK INGREDIENT - ANIMAL DRUG
Date: 20250108

ACTIVE INGREDIENTS: NITROFURAZONE 1 g/1 g

Nitrofurazone